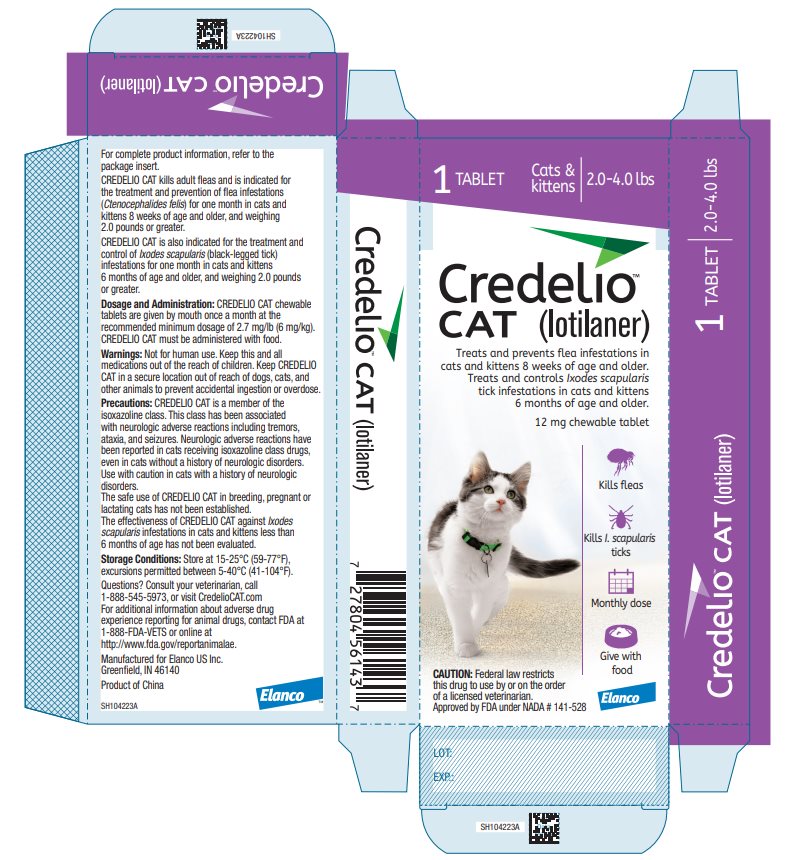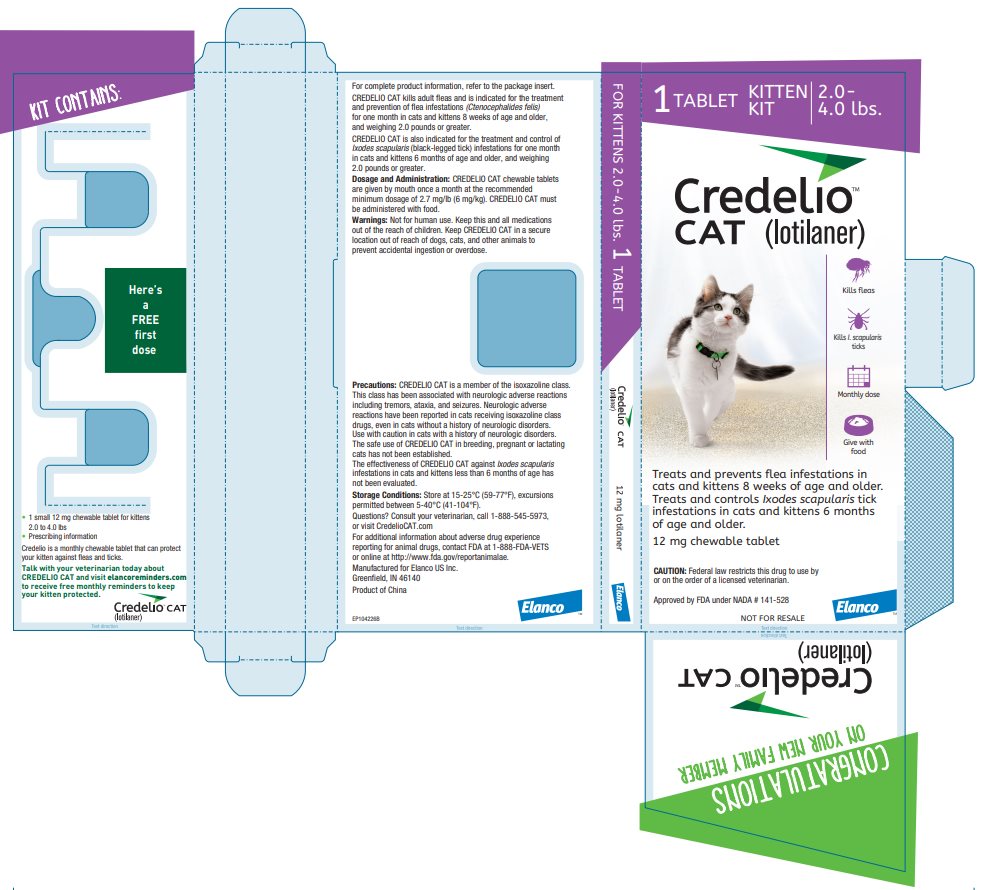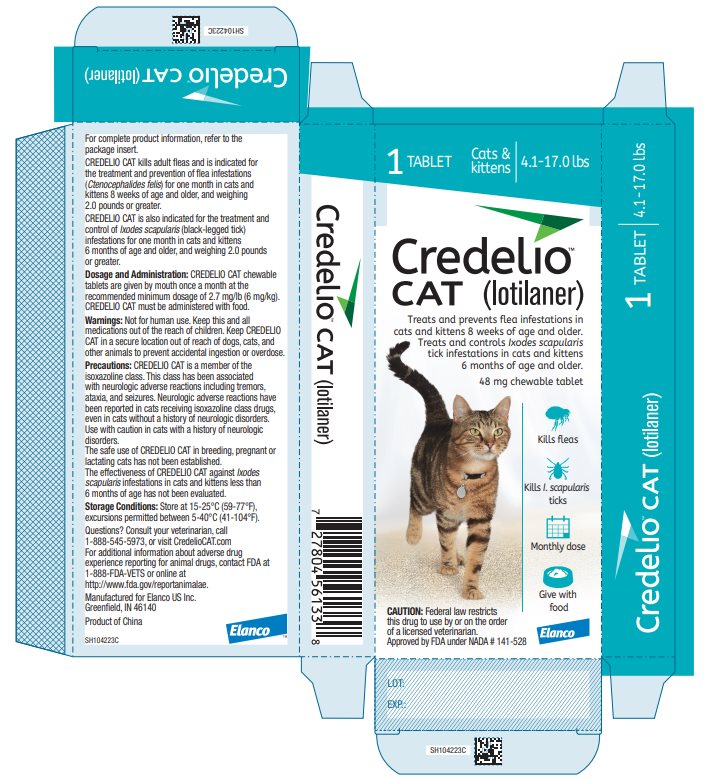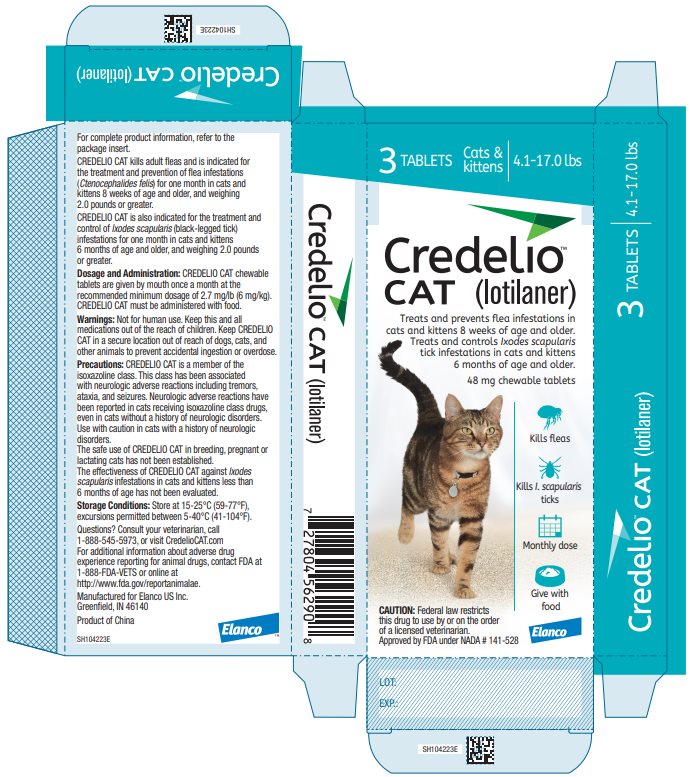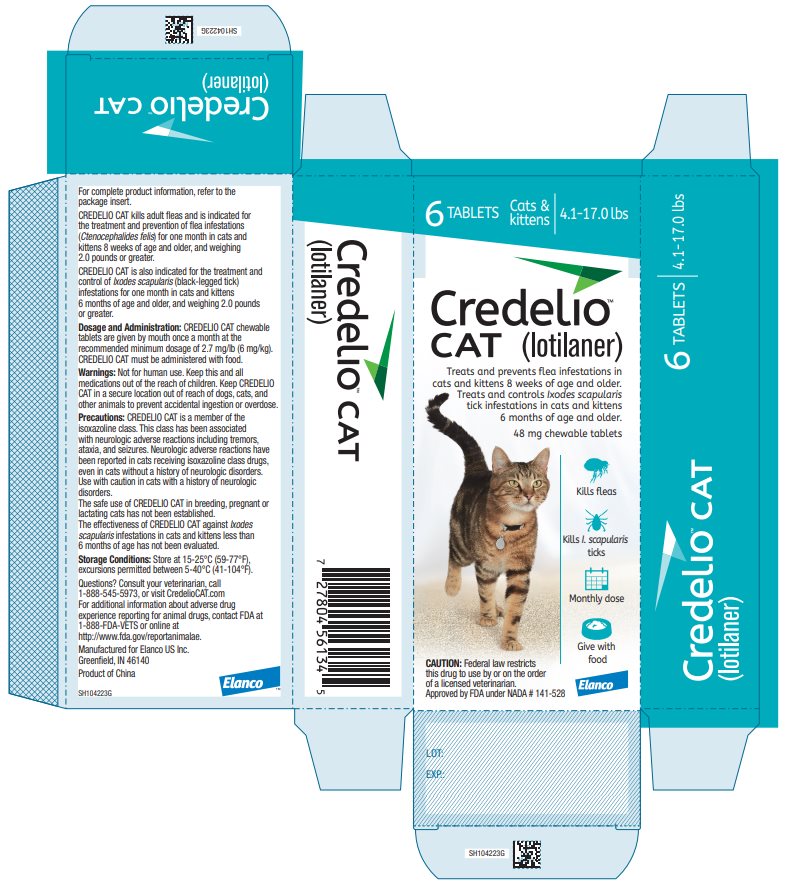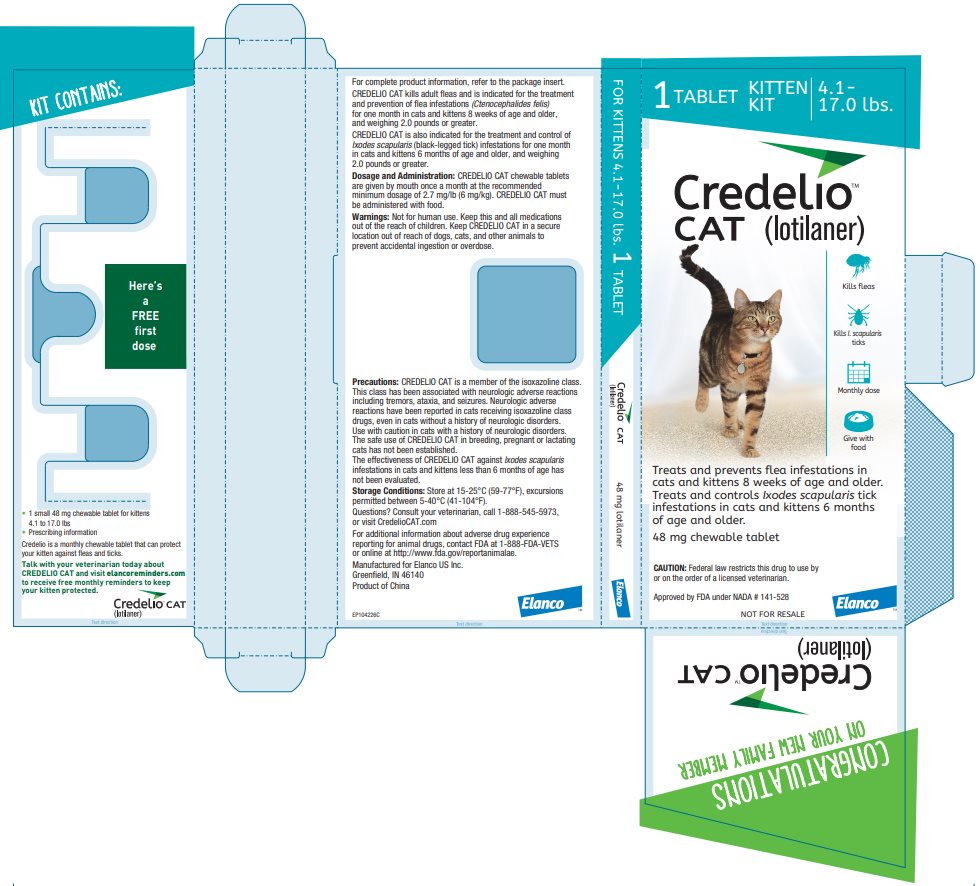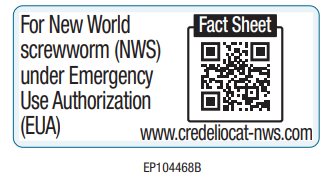 DRUG LABEL: Credelio
NDC: 58198-5487 | Form: TABLET, CHEWABLE
Manufacturer: Elanco US Inc.
Category: animal | Type: PRESCRIPTION ANIMAL DRUG LABEL
Date: 20260220

ACTIVE INGREDIENTS: Lotilaner 12 mg/1 1

Credelio™
CAT (lotilaner)

Chewable Tablets

For oral use in cats

Caution:

Federal law restricts this drug to use by or on the order of a licensed veterinarian.

Description:

CREDELIO CAT (lotilaner) is a chewable tablet for oral administration to cats and kittens according to their weight. Each chewable tablet is formulated to provide a minimum lotilaner dosage of 2.7 mg/lb (6 mg/kg).

Lotilaner has the chemical composition of 5-[(5S)-4,5-dihydro-5-(3,4,5-trichlorophenyl)-5-(trifluoromethyl)-3-isoxazolyl]-3-methyl-N-[2-oxo-2-[(2,2,2-trifluoroethyl)amino]ethyl]-2-thiophenecarboxamide.

Indications:

CREDELIO CAT kills adult fleas and is indicated for the treatment and prevention of flea infestations (Ctenocephalides felis) for one month in cats and kittens 8 weeks of age and older, and weighing 2.0 pounds or greater.

CREDELIO CAT is also indicated for the treatment and control of Ixodes scapularis (black-legged tick) infestations for one month in cats and kittens 6 months of age and older, and weighing 2.0 pounds or greater.

Dosage and Administration:

CREDELIO CAT is given orally once a month, at the minimum dosage of 2.7 mg/lb (6 mg/kg).

Dosage Schedule:

Body Weight | Lotilaner Per Chewable Tablet (mg) | Chewable Tablets Administered
2.0 to 4.0 lbs | 12 | One
4.1 to 17.0 lbs | 48 | One
Over 17.0 lbs | NA | Administer the appropriate combination of chewable tablets
NA = not applicable.

CREDELIO CAT must be administered with food (see Clinical Pharmacology).

Treatment with CREDELIO CAT can begin at any time of the year and can continue year-round without interruption.

Contraindications:

There are no known contraindications for the use of CREDELIO CAT.

Warnings:

Not for human use. Keep this and all drugs out of the reach of children.

Keep CREDELIO CAT in a secure location out of reach of dogs, cats, and other animals to prevent accidental ingestion or overdose.

Precautions:

Lotilaner is a member of the isoxazoline class. This class has been associated with neurologic adverse reactions including tremors, ataxia, and seizures. Neurologic adverse reactions have been reported in cats receiving isoxazoline class drugs, even in cats without a history of neurologic disorders. Use with caution in cats with a history of neurologic disorders.

The safety of CREDELIO CAT has not been established in breeding, pregnant and lactating cats (see Foreign Market Experience).

The effectiveness of CREDELIO CAT against Ixodes scapularis in kittens less than 6 months of age has not been evaluated.

Adverse Reactions:

In a well-controlled U.S. field study, which included 341 cats (228 cats treated with CREDELIO CAT and 113 cats treated with a topical active control), there were no serious adverse reactions.

Cats with Adverse Reactions in the Field Study

Adverse Reaction (AR) | CREDELIO CAT Group: Number (and Percent) of Cats with the AR (n=228) | Active Control Group: Number (and Percent) of Cats with the AR (n=113)
Weight Loss | 5 (2.2%) | 2 (1.8%)
Tachypnea | 3 (1.3%) | 0 (0.0%)
Vomiting | 3 (1.3%) | 1 (0.9%)
Diarrhea | 2 (0.9%) | 0 (0.0%)
Anorexia | 2 (0.9%) | 0 (0.0%)
Elevated blood urea nitrogen (BUN)* | 2 (0.9%) | 0 (0.0%)
*Two geriatric cats developed mildly elevated blood urea nitrogen (BUN) (42 to 58 mg/dL; reference range: 14 to 36 mg/dL) during the study. One of these cats, which had suspected pre-existing kidney disease, also developed a mildly elevated serum creatinine (2.5 mg/dL; reference range: 0.6 to 2.4 mg/dL) during the study.

Foreign Market Experience: The following adverse events were reported voluntarily during post-approval use of the product in cats in foreign markets: hyperactivity, pruritus, tachypnea, dyspnea, lethargy, vomiting, anorexia, hyperthermia, hypersalivation, tachycardia, mydriasis, tremors, ataxia, seizures, hepatopathy, anaphylactic reactions resulting in death, pancreatitis, immune mediated hemolytic anemia, and glomerulopathy.

Five 3- to 4-week-old nursing kittens (one litter of 2 kittens and one litter of 3) died within three days of the queens receiving CREDELIO CAT. Two pregnant cats spontaneously aborted or had fetal and perinatal deaths within a few days of receiving CREDELIO CAT.

Post-Approval Experience (2024)

The following adverse events are based on post-approval adverse drug experience reporting for CREDELIO CAT. Not all adverse events are reported to FDA/CVM. It is not always possible to reliably estimate the adverse event frequency or establish a causal relationship to product exposure using these data.

The following adverse events reported in cats are listed in decreasing order of reporting frequency:
Pruritus, vomiting, lethargy, behavioral changes (including hyperactivity, vocalization, and hiding), tachypnea, anorexia, muscle tremor, dyspnea, hyperthermia, and ataxia.

Contact Information

To report suspected adverse events, for technical assistance or to obtain a copy of the Safety Data Sheet (SDS), contact Elanco US Inc. at 1-888-545-5973.

For additional information about adverse drug experience reporting for animal drugs, contact FDA at 1-888-FDA-VETS or http://www.fda.gov/reportanimalae.

Clinical Pharmacology:

Following oral administration of 26 mg/kg (the maximum labeled dose), peak lotilaner concentrations were achieved in most cats at the 24-hour sampling point. Cats 3 months of age had a shorter elimination half-life (average of 7.5 days) than at 7 months of age (average of 32 days).

Due to reduced drug bioavailability in the fasted state, CREDELIO CAT must be administered with a meal or within 30 minutes after feeding.

Mode of Action:

Lotilaner is an ectoparasiticide belonging to the isoxazoline group. Lotilaner inhibits insect and acarine gamma-aminobutyric acid (GABA)-gated chloride channels. This inhibition blocks the transfer of chloride ions across cell membranes, which results in uncontrolled neuromuscular activity leading to death of insects and acarines. The selective toxicity of lotilaner between insects and acarines and mammals may be inferred by the differential sensitivity of the insects and acarines’ GABA receptors versus mammalian GABA receptors.

Effectiveness:

In a well-controlled laboratory study, CREDELIO CAT began to kill fleas six hours after administration, with greater than 98% of fleas killed within 12 hours after administration. In another well-controlled laboratory study, CREDELIO CAT demonstrated 100% effectiveness against adult fleas 24 hours after administration or infestation for 35 days.

In a 90-day well-controlled U.S. field study conducted in cats with existing flea infestations of varying severity, the effectiveness of CREDELIO CAT against fleas on Days 30, 60 and 90 compared to baseline was 98.5%,100% and 100%, respectively. Cats with signs of flea allergy dermatitis showed improvement in erythema, papules, scaling, alopecia, dermatitis/pyodermatitis, and pruritus as a direct result of eliminating fleas.

In a well-controlled laboratory study, CREDELIO CAT killed fleas before they could lay eggs, thus preventing subsequent flea infestations after the start of treatment of existing flea infestations for 30 days.

In well-controlled laboratory studies, CREDELIO CAT demonstrated >97% effectiveness against Ixodes scapularis ticks 72 hours after administration or infestation for 31 days.

Palatability: In the U.S. field study, which included 648 doses administered to 225 cats, 21.1% of the doses were voluntarily consumed when CREDELIO CAT was offered by hand, on the floor, or in an empty bowl, an additional 25.8% of doses were voluntarily consumed when CREDELIO CAT was offered with food, and 52.6% of doses required placement of the chewable tablet in the back of the cat’s mouth.

Owners were unable to administer CREDELIO CAT for 0.5% of doses.

Animal Safety:

In a margin of safety study, CREDELIO CAT was administered orally to 24 (8 cats/group) 8-week-old cats at 1, 3 and 5X the maximum labeled dose of 26 mg/kg every 28 days for eight consecutive doses. The 8 cats in the control group (0X) were untreated.

There were no clinically-relevant, treatment-related effects on physical and neurologic examinations or gross pathology. Dry food consumption was reduced in male cats in all treated groups compared to control cats. Body weights of male cats in the 3X group were less than the control male cats. Vomiting occurred post-dosing in cats in all groups, including the control group, but was increased in the 5X group. At multiple time points, neutrophil counts were decreased (750-2710/μL; low end of normal: approximately 2800/μL) in cats in all treated groups compared to control cats, including in a cat in the 3X group that died during anesthesia to obtain the electrocardiogram (ECG). From Days 28 to 92, two and three female cats in the 3X and 5X group, respectively, had elevations in blood urea nitrogen (BUN) at least at one time point (37-43 mg/dL; high end of normal: 36 mg/dL). Three cats each in the control, 1X and 5X groups and six cats in the 3X group had minimal, usually unilateral, tubular regeneration of the kidneys. One cat each in the control, 1X and 5X groups and four cats in the 3X group had minimal generalized lymphoid depletion of the thymus. Four of the five cats in the two high-dose groups (3X and 5X) with the thymus changes also had neutropenia at 25% or more of the time points.

Blood concentrations of lotilaner confirmed systemic exposure in all cats administered lotilaner, although the exposure was less than dose proportional.

Storage Information:

Store at 15-25°C (59 -77°F), excursions permitted between 5 to 40°C (41 to 104°F).

How Supplied:

CREDELIO CAT is available in two chewable tablet sizes for use in cats: 12 and 48 mg lotilaner. Each chewable tablet size is available in color-coded packages containing 1 chewable tablet. The 48 mg chewable tablet size is also available in color-coded packages containing 3 or 6 chewable tablets.

Approved by FDA under NADA # 141-528

Manufactured for:
Elanco US Inc
Greenfield, IN 46140 USA

CredelioCAT.com

Credelio, Elanco and the diagonal bar logo are trademarks of Elanco or its affiliates. © 2024 Elanco or its affiliates

Rev. date November 2024

PA104223X

ElancoTM

Fact Sheet for Veterinarians: Emergency Use Authorization of Credelio™ CAT (lotilaner)

CredelioTM
CAT (lotilaner)

Chewable Tablets
For oral use in cats

Original EUA Authorized Date: 11/21/2025

Emergency Use Authorization for CREDELIO CAT (lotilaner) for New World Screwworm (NWS)

The U.S. Food and Drug Administration (FDA) has issued an Emergency Use Authorization (EUA) for the emergency use of the approved product CREDELIO CAT (lotilaner) for the treatment of infestations caused by NWS (Cochliomyia hominivorax) larvae (myiasis) in cats and kittens. CREDELIO CAT is not approved for this use.

CREDELIO CAT is approved for other uses [On December 9, 2019, CREDELIO CAT was approved to kill adult fleas and is indicated for the treatment and prevention of flea infestations (Ctenocephalides felis) for one month in cats and kittens 8 weeks of age and older, and weighing 2.0 pounds or greater. On April 12, 2021, CREDELIO CAT received a supplemental approval for the treatment and control of tick infestations [Ixodes scapularis (black-legged tick)] for one month in cats and kittens 6 months of age and older, and weighing 2.0 pounds or greater.] .

Limitations of Authorized Use

CREDELIO CAT (lotilaner) is authorized for this use only for the duration of the declaration that circumstances exist justifying the authorization of the emergency use of CREDELIO CAT (lotilaner) under section 564(b)(1) of the Federal Food, Drug, and Cosmetic Act (FD&C Act), 21 U.S.C. § 360bbb-3(b)(1), unless the authorization is terminated or revoked sooner.

Justification for Emergency Use of Animal Drugs for NWS

The Secretary of the U.S. Department of Health and Human Services (HHS) has:

- Determined that there is a significant potential for a public health emergency that has a significant potential to affect national security or the health and security of United States citizens living abroad and that involves NWS (Cochliomyia hominivorax) [See U.S. Department of Health and Human Services, Declaration of Emergency Pursuant to the Federal Food, Drug, and Cosmetic Act for New World Screwworm, August 20, 2025: https://www.federalregister.gov/documents/2025/08/20/2025-15918/declaration-of-emergency-pursuant-to-the-federal-food-drug-and-cosmetic-act-for-new-world-screwworm] .
- Declared that circumstances exist justifying the authorization of emergency use of animal drugs to treat or prevent NWS myiasis in animals.

An EUA is an FDA authorization for the emergency use of an unapproved product or unapproved use of an approved product (i.e., drug, biological product, or device) in the United States under certain circumstances including, but not limited to, when the Secretary of HHS declares circumstances exist justifying the product’s emergency authorization, based on a determination, including but not limited to, a public health emergency or a significant potential for a public health emergency that may affect national security and that involves a biological agent [Emergency Use Authorization of Medical Products and Related Authorities | FDA (https://www.fda.gov/regulatory-information/search-fda-guidance-documents/emergency-use-authorization-medical-products-and-related-authorities)] .

Criteria for issuing this EUA include:

- The biological agent can cause a serious or life-threatening disease or condition;
- Based on the available scientific evidence (including data from adequate and well-controlled clinical trials, if available), it is reasonable to believe that:
  - The product may be effective in diagnosing, treating, or preventing the serious or life-threatening disease or condition; and
  - The known and potential benefits of the product - when used to treat such disease or condition - outweigh the known and potential risks of the product;
- There is no adequate, approved, and available alternative to the product for treating the serious or life-threatening disease or condition [FDA’s “New World Screwworm: Information for Veterinarians”: https://www.fda.gov/animal-veterinary/safety-health/new-world-screwworm-information-veterinarians] .

Caution: Federal law restricts this drug to use by or on the order of a licensed veterinarian.

Description:

Refer to the package insert for full Description information.

Dosage and Administration:

CREDELIO CAT is given orally at the minimum dosage of 2.7 mg/lb (6 mg/kg).

Dosage Schedule:

Body Weight | Lotilaner Per Chewable Tablet (mg) | Chewable Tablets Administered
2.0 to 4.0 lbs | 12 | One
4.1 to 17.0 lbs | 48 | One
Over 17.0 lbs | NA | Administer the appropriate combination of chewable tablets

CREDELIO CAT must be administered with food.

CREDELIO CAT is not available as scored tablets. The effectiveness of the administration of less than full tablets has not been evaluated.

Risk-Benefit Consideration for Cats on Other Isoxazolines:

If a cat is currently receiving another isoxazoline product for routine ectoparasite control, veterinarians should consider administering CREDELIO CAT to cats diagnosed with NWS myiasis based on a risk-benefit assessment and the emergency nature of NWS myiasis treatment.

Information Supporting Emergency Use Authorization

Based on the scientific evidence available to FDA, including data from published scientific literature, it is reasonable to believe that CREDELIO CAT may be effective for the treatment of infestations caused by NWS (Cochliomyia hominivorax) larvae (myiasis) in cats and kittens, and the known and potential benefits of CREDELIO CAT outweigh the known and potential risks.

A study conducted by Han and Yasmin [Han, HS, Yasmin, L (2020). Chrysomya bezziana (Diptera: Calliphoridae) infestation in two Malaysian cats treated with oral lotilaner. Vet Dermatol, 31:335-e87.] evaluated the effectiveness of lotilaner [Same formulation as CREDELIO CAT.] for the treatment of naturally acquired Old World screwworm (OWS, Chrysomya bezziana) myiasis in cats in Malaysia. Two client-owned cats with active myiasis caused by Chrysomya bezziana larvae were enrolled. The cats included a 3-year-old male intact cat with a wound on the left hind paw and a 9-year-old male neutered cat with a wound on the right cervical neck region. Both cats received a single oral administration of lotilaner at doses of either 6 or 26 mg/kg body weight, following the dose bands for the approved flea and tick indications. The study was a case report and did not include a control group.

After treatment, both cats were hospitalized for 10 and 11 days and wounds were cleansed and flushed with saline solution until re-epithelization occurred. The study demonstrated 100% larvicidal effectiveness against OWS (Chrysomya bezziana) at 24 hours post-treatment in both cats. There were no adverse reactions during the study.

A study conducted by do Vale et al. [do Vale TL, Costa AR, Miranda LM, Silva GF, Silva NCS, Lima TB, Chaves DP, Sager H, Lasmar PVF, Costa-Junior LM. Efficacy of lotilaner against myiasis caused by Cochliomyia hominivorax (Diptera: Calliphoridae) in naturally infested dogs. Parasit Vectors. 2023;16(1):86.] evaluated the effectiveness of CREDELIO (lotilaner) for the treatment of naturally acquired NWS myiasis in dogs in Brazil. Eleven client-owned dogs with active myiasis caused by Cochliomyia hominivorax larvae were enrolled based on lesion severity and larval burden. All dogs received a single oral administration of CREDELIO using the dose bands for the approved flea and tick indications. The study did not include a control group. After treatment, the dogs were kept in individual kennels with a removable tray. The dogs were observed 2- and 6-hours post-treatment, at which times expelled larvae were collected and quantified. At 24 hours post-treatment, the remaining larvae were mechanically removed from the wound and counted. The study demonstrated 100% overall effectiveness (number of expelled live and dead larvae and dead larvae mechanically removed) against Cochliomyia hominivorax larvae at 24 hours post-treatment with expulsion of larvae of 80.5% and 93% at 2 and 6 hours after treatment, respectively. The mean larvicidal effectiveness was 41.1% at 24 hours. There were no adverse reactions during the study.

There are several limitations of the data supporting the benefits of CREDELIO CAT for the treatment of NWS infestations, as the available study in cats was conducted against a different parasite species (OWS). The Han and Yasmin study was conducted in a limited population of two cats naturally infested with Old World screwworm (Chrysomya bezziana) in Malaysia, and the inferential value to the United States population and NWS species is unknown. Additionally, the case report design, lack of a control group, and demonstrated effectiveness in a different parasite species (Chrysomya bezziana vs. Cochliomyia hominivorax) limits the ability to define a pure treatment effect. The do Vale et al. study was conducted in a limited population of eleven naturally infested dogs in Brazil, and the inferential value to cats is unknown; however, the study used the approved lotilaner dose for the flea and tick indications. In that study, the primary mechanism of action against Cochliomyia hominivorax appears to be live larval expulsion. Additionally, the use of mechanical removal coupled with the lack of a control group confound the ability to define a pure treatment effect.

The available clinical data supporting the effectiveness of CREDELIO CAT against OWS (Chrysomya bezziana) larvae, and the effectiveness data for lotilaner in dogs against NWS, along with the established safety profile, support the potential benefit of CREDELIO CAT in the authorized patient population for the treatment of infestations caused by NWS larvae.

Contraindications:

There are no known contraindications for the use of CREDELIO CAT.

Warnings:

Not for human use. Keep this and all drugs out of the reach of children. Keep CREDELIO CAT in a secure location out of reach of dogs, cats, and other animals to prevent accidental ingestion or overdose.

Precautions:

Lotilaner is a member of the isoxazoline class. This class has been associated with neurologic adverse reactions including tremors, ataxia, and seizures. Neurologic adverse reactions have been reported in cats receiving isoxazoline class drugs, even in cats without a history of neurologic disorders. Use with caution in cats with a history of neurologic disorders.

The safe use of CREDELIO CAT in breeding, pregnant, or lactating cats has not been evaluated (see Foreign Market Experience on package insert).

The safety of CREDELIO CAT has not been evaluated in cats less than 8 weeks of age or less than 2.0 lbs.

Adverse Reactions:

Refer to the package insert for full prescribing information, including Animal Safety, Adverse Reactions, and Post-Approval Experience.

As described in the Letter of Authorization, veterinary facilities and veterinarians must report all SERIOUS ADVERSE EVENTS* potentially related to CREDELIO CAT use under this EUA (1) by contacting Elanco US Inc. at 1-888-545-5973, (2) by downloading and submitting Form FDA 1932a available at https://www.fda.gov/reportanimalae, or (3) contacting FDA at 1-888-FDA-VETS to request this form.

When reporting adverse events on Form FDA 1932a, include the following elements when applicable and/or available:

- Patient demographics (e.g., age, species and breed, sex, weight) • The statement “CREDELIO CAT use for NWS under an EUA” under the “Describe Adverse Event/Product Problem/Event Use Error” heading
- Information about the serious adverse event (e.g., signs and symptoms, test/laboratory data, timing of drug administration in relation to the occurrence of the event, duration of the event, treatment required to mitigate the event, evidence of event improvement/disappearance after stopping/reducing the dosage, evidence of reappearance after reintroduction, clinical outcomes).
- Patient’s pre-existing medical conditions and use of concomitant products
- Information about the product (e.g., dosage, route of administration, NDC#)

*Serious adverse events are defined as:

- Death
- A life-threatening adverse event
- An event that causes an abortion, stillbirth, or infertility
- A congenital anomaly or birth defect in offspring of treated animals
- A prolonged or permanent disability (e.g., persistent or significant incapacity or disruption of normal life functions)
- An event that requires professional intervention (e.g., important medical events that may require a medical/surgical intervention to prevent a death, life-threatening event, hospitalization, disability)

Reporting of lack of effectiveness, nonserious adverse events, or product quality defects is strongly encouraged via the mechanisms and including the information identified above for SERIOUS ADVERSE EVENTS.

Additional Information for Veterinarians:

Veterinary facilities and veterinarians will ensure that they are aware of and adhere to the terms of the Letter of Authorization. Fact Sheets will be made available to veterinarians.

Veterinary facilities and veterinarians will ensure that the client is aware that the drug is authorized for emergency use, but not approved, for the treatment of NWS myiasis and advise the client of the risks, benefits, and any alternatives.

Veterinary facilities will maintain health records that include the following information: client name, patient name, patient age, disease manifestation, number of doses prescribed or administered per patient, lot number prescribed or administered, and other drugs co-administered. The records shall be maintained in a manner that allows veterinary facilities to identify in a reasonable time which patients received drugs subject to this EUA.

Veterinary facilities will maintain any health records for the authorized use in this Letter of Authorization for at least two years following the termination or revocation of the EUA, or until notified by HHS, or FDA, whichever is sooner. Such records will be made available to Elanco US Inc., HHS, and FDA for inspection upon request.

Additional Information for Client (e.g., Animal Owner):

The lifecycle for C. hominivorax is as short as 21 days and wounds can be rapidly infested. Proper wound care and management practices are essential for preventing NWS myiasis. Cats may become reinfested following treatment.

Clients should be advised that:

- Gloves should be worn if cleaning the wound or the cat’s bedding or disposing of larvae.
- Cats should be housed to prevent exposure to NWS flies until wounds have fully healed.
- Live larvae may exit the wound and be deposited on bedding or areas where the cat sits or lies after treatment.
- If expelled larvae are seen, clients should place the larvae in a sealed container with rubbing alcohol.
- If there is worsening of the wound, the client should contact the veterinarian.

How Supplied:

CREDELIO CAT is available in two chewable tablet sizes for use in cats: 12 and 48 mg lotilaner. Each chewable tablet size is available in color-coded packages of 1 chewable tablet. The 48 mg chewable tablet size is also available in color-coded packages containing 3 or 6 chewable tablets.

Storage Information:

Store at 15-25°C (59-77°F), excursions permitted between 5 to 40°C (41 to 104°F).

Manufactured for:
Elanco US Inc.
Greenfield, IN 46140 USA
CredelioCAT.com
November 2025

ElancoTM

PA104468X

W1a

Principal Display Panel - 12 mg Box Label

1 TABLET

Cats &
Kittens

2.0-4.0 lbs

Credelio™
CAT (lotilaner)

Treats and prevents flea infestations in
cats and kittens 8 weeks of age and older.
Treats and controls Ixodes scapularis
tick infestations in cats and kittens
6 months of age and older.

12 mg chewable tablet

Kills fleas

Kills I. scapularis
ticks

Monthly dose

Give with
food

CAUTION: Federal law restricts
this drug to use by or on the order
of a licensed veterinarian.

Approved by FDA under NADA # 141-528

Elanco

1 TABLET

KITTEN
KIT

2.0 -
4.0 lbs.

Credelio™
CAT (lotilaner)

Treats and prevents flea infestations in
cats and kittens 8 weeks of age and older.
Treats and controls Ixodes scapularis tick
infestations in cats and kittens 6 months
of age and older.

12 mg chewable tablet

Kills fleas

Kills I. scapularis
ticks

Monthly dose

Give with
food

CAUTION: Federal law restricts this drug to use by
or on the order of a licensed veterinarian.

Approved by FDA under NADA # 141-528

ElancoTM

NOT FOR RESALE

Principal Display Panel - 48 mg Box Label

1 TABLET

Cats &
Kittens

4.1-17.0 lbs

Credelio™
CAT (lotilaner)

Treats and prevents flea infestations in
cats and kittens 8 weeks of age and older.
Treats and controls Ixodes scapularis
tick infestations in cats and kittens
6 months of age and older.

48 mg chewable tablet

Kills fleas

Kills I. scapularis
ticks

Monthly dose

Give with
food

CAUTION: Federal law restricts
this drug to use by or on the order
of a licensed veterinarian.

Approved by FDA under NADA # 141-528

Elanco

3 TABLETS

Cats &
Kittens

4.1-17.0 lbs

Credelio™
CAT (lotilaner)

Treats and prevents flea infestations in
cats and kittens 8 weeks of age and older.
Treats and controls Ixodes scapularis
tick infestations in cats and kittens
6 months of age and older.

48 mg chewable tablet

Kills fleas

Kills I. scapularis
ticks

Monthly dose

Give with
food

CAUTION: Federal law restricts
this drug to use by or on the order
of a licensed veterinarian.

Approved by FDA under NADA # 141-528

Elanco

6 TABLETS

Cats &
Kittens

4.1-17.0 lbs

Credelio™
CAT (lotilaner)

Treats and prevents flea infestations in
cats and kittens 8 weeks of age and older.
Treats and controls Ixodes scapularis
tick infestations in cats and kittens
6 months of age and older.

48 mg chewable tablet

Kills fleas

Kills I. scapularis
ticks

Monthly dose

Give with
food

CAUTION: Federal law restricts
this drug to use by or on the order
of a licensed veterinarian.

Approved by FDA under NADA # 141-528

Elanco

1 TABLET

KITTEN
KIT

4.1 -
17.0 lbs.

Credelio™
CAT (lotilaner)

Treats and prevents flea infestations in
cats and kittens 8 weeks of age and older.
Treats and controls Ixodes scapularis tick
infestations in cats and kittens 6 months
of age and older.

48 mg chewable tablet

Kills fleas

Kills I. scapularis
ticks

Monthly dose

Give with
food

CAUTION: Federal law restricts this drug to use by
or on the order of a licensed veterinarian.

Approved by FDA under NADA # 141-528

ElancoTM

NOT FOR RESALE

Principal Display Panel – Emergency Use Authorization

For New World
screwworm (NWS)
under Emergency
Use Authorization
(EUA)

Fact Sheet

www.credeliocat-nws.com

EP104468B